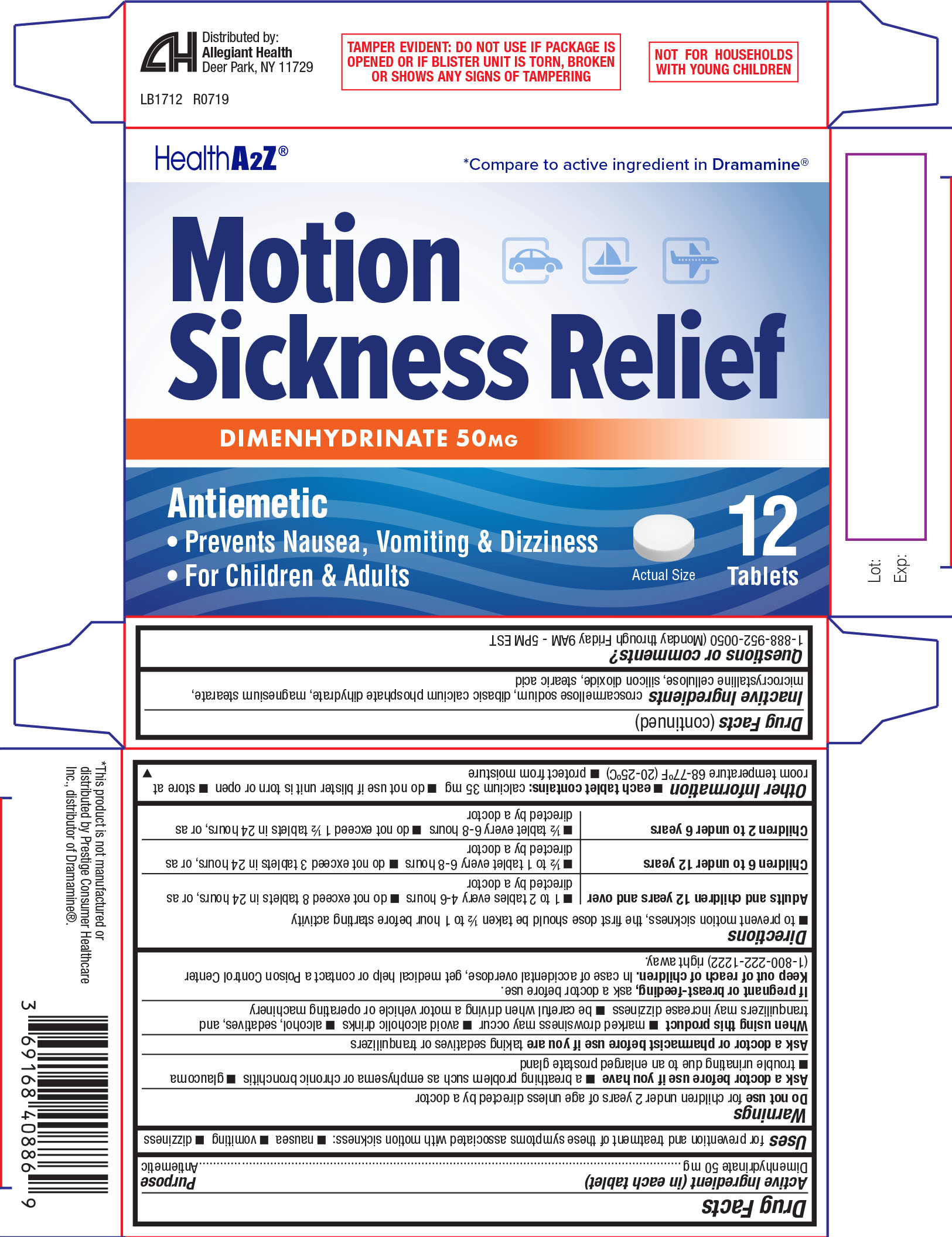 DRUG LABEL: Motion Sickness Relief
NDC: 69168-408 | Form: TABLET
Manufacturer: Allegiant Health
Category: otc | Type: HUMAN OTC DRUG LABEL
Date: 20191212

ACTIVE INGREDIENTS: DIMENHYDRINATE 50 mg/1 1
INACTIVE INGREDIENTS: SILICON DIOXIDE; MAGNESIUM STEARATE; CELLULOSE, MICROCRYSTALLINE; DIBASIC CALCIUM PHOSPHATE DIHYDRATE; CROSCARMELLOSE SODIUM; STEARIC ACID

Dramamine Original Formula

Active ingredient (in each tablet)

Dimenhydrinate 50 mg

Purpose

Antiemetic

Use

for prevention and treatment of these symptoms associated with motion sickness:

- nausea
- vomiting
- dizziness

Warnings

Do not use

for children under 2 years of age unless directed by a doctor

Ask a doctor before use if you have

- a breathing problem such as emphysema or chronic bronchitis
- glaucoma
- trouble urinating due to an enlarged prostate gland

Ask a doctor or pharmacist before use if you are

taking sedatives or tranquilizers

When using this product

- marked drowsiness may occur
- avoid alcoholic drinks
- alcohol, sedatives, and tranquilizers may increase dizziness
- be careful when driving a motor vehicle or operating machinery

If pregnant or breast-feeding,

ask a doctor before use.

Keep out of reach of children.

In case of accidental overdose, get medical help or contact a Poison Control Center (1-800-222-1222) right away.

Directions

- to prevent motion sickness, the first dose should be taken ½ to 1 hour before starting activity

Adults and children 12 years and over | - 1 to 2 tables every 4-6 hours - do not exceed 8 tablets in 24 hours, or as directed by a doctor
Children 6 to under 12 years | - ½ to 1 tablet every 6-8 hours - do not exceed 3 tablets in 24 hours, or as directed by a doctor
Children 2 to under 6 years | - ½ tablet every 6-8 hours - do not exceed 1 ½ tablets in 24 hours, or as directed by a doctor

Other information

- each tablet contains: calcium 35mg
- do not use ifblister unit is torn or open
- store at room temperature 68-77ºF (20-25ºC)
- protect from moisture

Inactive ingredients

croscarmellose sodium, dibasic calcium phosphate dihydrate, magnesium stearate, microcrystalline cellulose, silicon dioxide, stearic acid

Questions or comments?

1-888-952-0050 (Monday through Friday 9AM - 5PM EST)

PRINCIPAL DISPLAY PANEL

Motion Sickness Relief